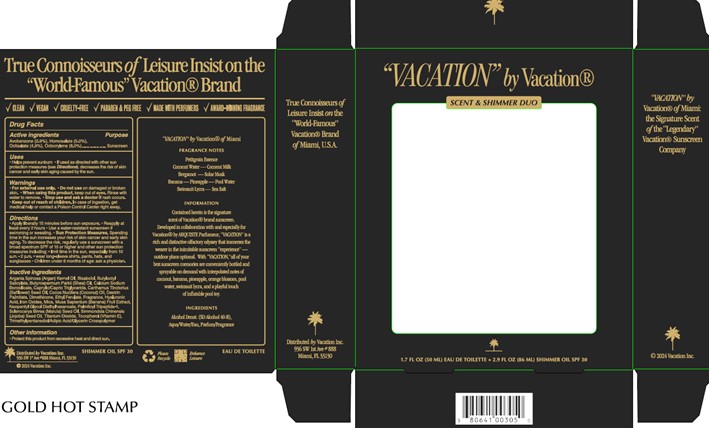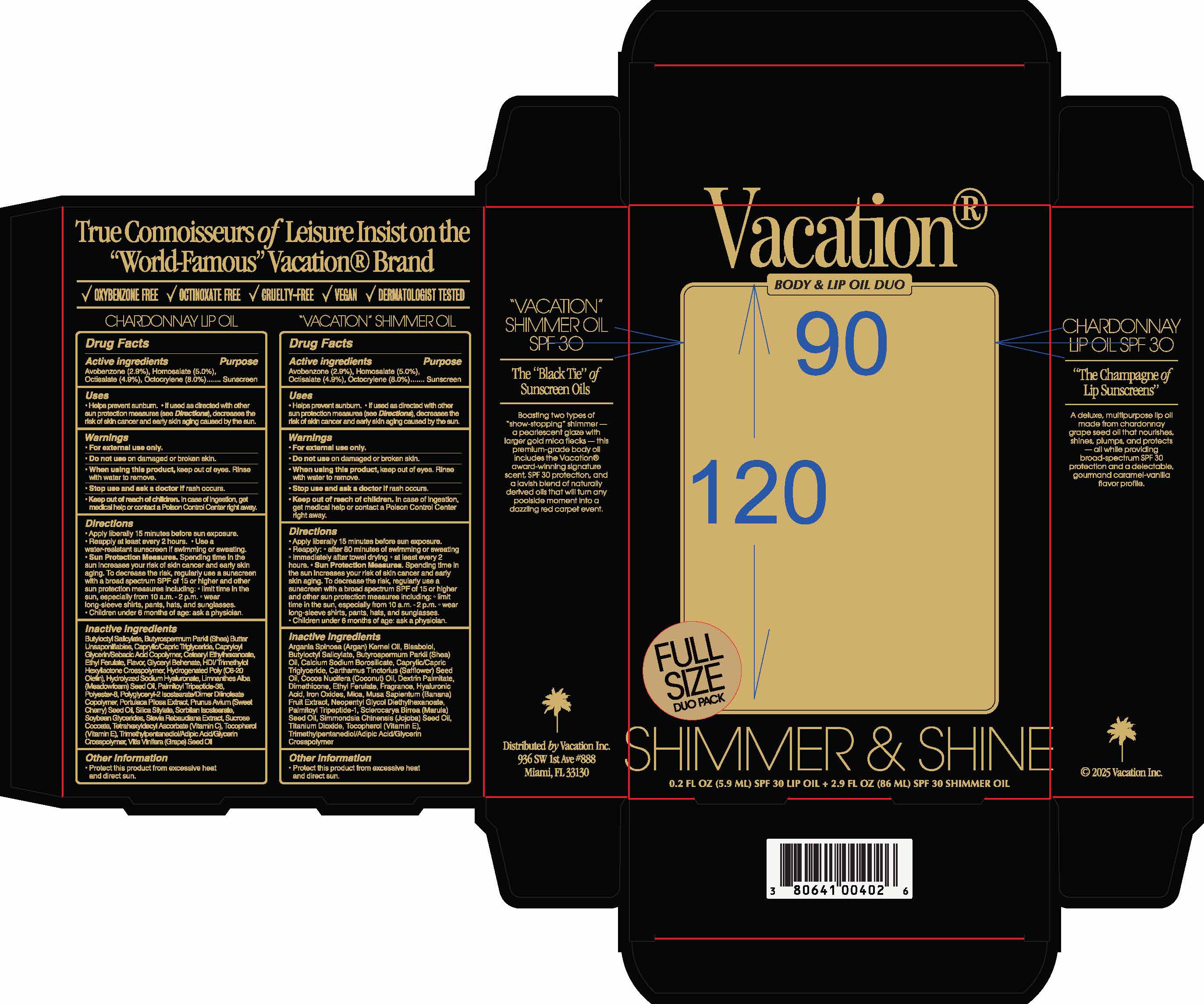 DRUG LABEL: Shimmer Oil
NDC: 80641-015 | Form: OIL
Manufacturer: Vacation Inc.
Category: otc | Type: HUMAN OTC DRUG LABEL
Date: 20250418

ACTIVE INGREDIENTS: AVOBENZONE 2.9 g/100 mL; OCTOCRYLENE 8 g/100 mL; OCTISALATE 4.9 g/100 mL; HOMOSALATE 5 g/100 mL
INACTIVE INGREDIENTS: BUTYLOCTYL SALICYLATE

Vacation Shimmer Body Oil

Dosage and Administration

Apply liberally 15 minutes before sun exposure

Reapply at least every 2 hours

Use a water resistant sunscreen if swimming or sweating

Warnings

For external use only

Do not use on damaged or broken skin

When using this product, keep out of eyes. Rinse with water to remove.

Stop use and ask a doctor is rash occurs

Indications and Usage

Helps prevent sunburn

If used as directed with other sun protection measures (see Directions), decreases the risk of skin cancer and early skin aging caused by the sun

Keep out of reach of children

In case of ingestion, get medical help or contact a Poison Control Center right away

Purpose

Sunscreen

Inactives

Argania Spinosa Kernel Oil, Bisabolol, Butyloctyl Salicylate, Butyrospermum Parkii (Shea) Oil, Calcium Sodium Borosilicate

Caprylic/Capric Triglyceride, Carthamus Tinctorius (Safflower) Seed Oil, Cocos Nucifera (Coconut) Oil, Dextrin Palmitate, Dimethicone, Ethyl Ferulate, Fragrance, Hyaluronic Acid, Iron Oxides, Mica, Musa Sapientum (Banana) Fruit Extract, Neopentyl Glycol, Diethylhexanoate, Palmitoyl Tripeptide-1, Sclerocarya Birrea Seed Oil, Simmondsia Chinensis (Jojoba) Seed Oil, Titanium Dioxide

Tocopherol, Trimethylpentanediol/Adipic Acid/Glycerin Crosspolymer